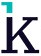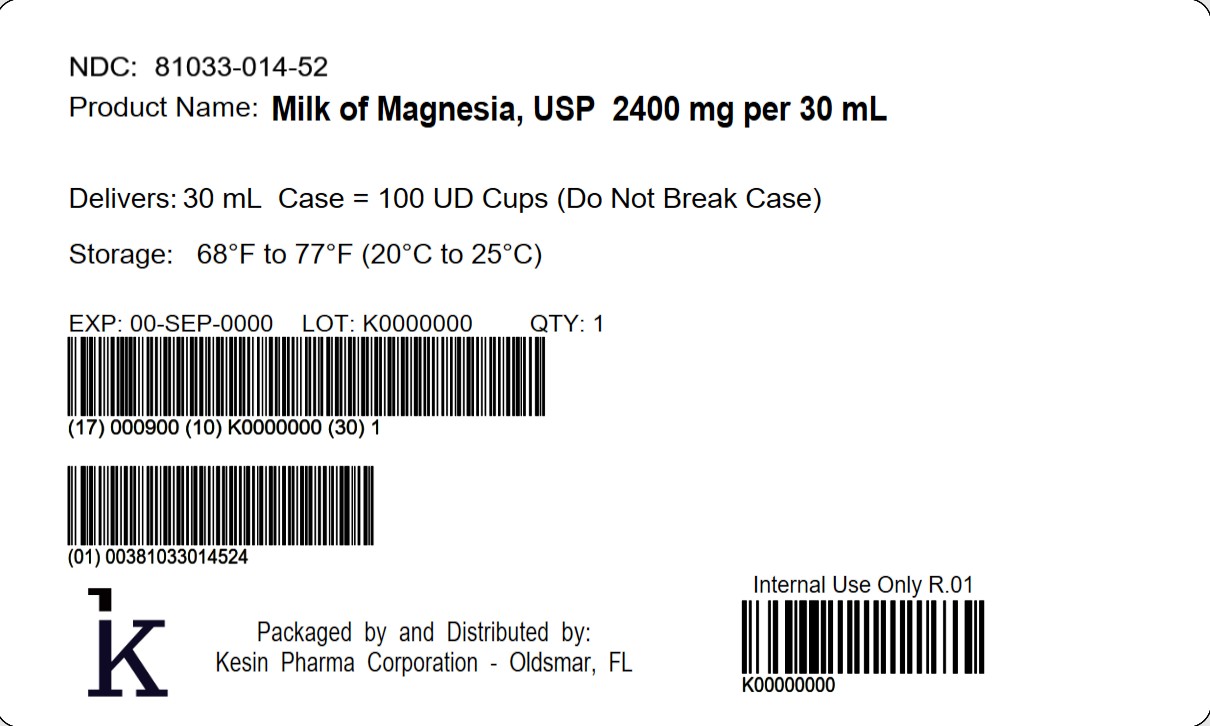 DRUG LABEL: Milk of Magnesia
NDC: 81033-014 | Form: SUSPENSION
Manufacturer: Kesin Pharma Corporation
Category: otc | Type: HUMAN OTC DRUG LABEL
Date: 20250923

ACTIVE INGREDIENTS: MAGNESIUM HYDROXIDE 400 mg/5 mL
INACTIVE INGREDIENTS: SILICA; METHYLPARABEN; GLYCERIN; PROPYLENE GLYCOL; WATER; SUCRALOSE; PROPYLPARABEN; SORBITOL; XANTHAN GUM

Milk of Magnesia

Drug Facts

Active ingredient (in each 5 mL)

Magnesium hydroxide 400 mg

Purpose

Saline laxative

Uses

As an Antacid:

- heartburn
- upset/sour stomach
- acid indigestion

As a Laxative (usually within ½ to 6 hours):

- occasional constipation (irregularity)

Warnings

Ask a doctor before use if you have

- kidney disease
- a magnesium-restricted diet
- stomach pain, nausea, or vomiting
- a sudden change in bowel habits that lasts over 14 days

Ask a doctor or pharmacist before use if you are taking a prescription drug. This product may interact with certain prescription drugs.

Stop use and ask a doctor if

- you have rectal bleeding or no bowel movement after using this product. These could be signs of a serious condition.
- you need to use a laxative for more than 1 week

PREGNANCY OR BREAST FEEDING

If pregnant or breast-feeding,ask a health professional before use.

Keep out of reach of children. In case of overdose, get medical help or contact a Poison Control Center right away.

Directions

As an Antacid:

- do not exceed the maximum recommended daily dose in a 24 hour period
- shake well before use
- can be taken with water
- mL = milliliter

Age | Dose
adults and children 12 years of age and over | 5 mL to 15 mL (1 to 3 teaspoonfuls)
children under 12 years of age | ask a doctor

As a Laxative

- do not exceed the maximum recommended daily dose of 60 mL in a 24 hour period
- shake well before use
- dose may be taken once a day preferably at bedtime, in divided doses, or as directed by a doctor. Drink a full glass (8 oz.) of liquid with each dose.
- mL = milliliter; TBSP = Tablespoon

Age | Dose
adults and children 12 years and older | 30 mL (2 TBSP) to 60 mL (4 TBSP)
children 6 to 11 years of age | 15 mL (1 TBSP) to 30 mL (2 TBSP)
children under 6 years | ask a doctor

Other information

- each teaspoonful (5 mL) contains: magnesium 400 mg
- store at 20°C to 25°C (68°F to 77°F).
- Avoid freezing
- Protect from light
- Milk of Magnesia, USP is a milky-white cherry flavored suspension supplied in the following oral dosage forms:

NDC 81033-014-30: 30 mL unit-dose cup

NDC 81033-014-52: Case containing 100 unit-dose cups of 30 mL each.

Inactive ingredients

cherry flavor, fumed silica, glycerin, methylparaben, propylene glycol, propylparaben, purified water, sorbitol solution, sucralose, xanthan gum

Questions or comments?

Call 1-833-537-4679

Distributed by:

Kesin Pharma

Oldsmar, FL 34677

PIS-014-V01

Rev. 09/2025

PRINCIPAL DISPLAY PANEL - 30 mL Cup Tray Label

NDC 81033-014-52

Milk of Magnesia, USP 2400 mg per 30 mL

Delivers 30 mL

Case = 100 UD Cups